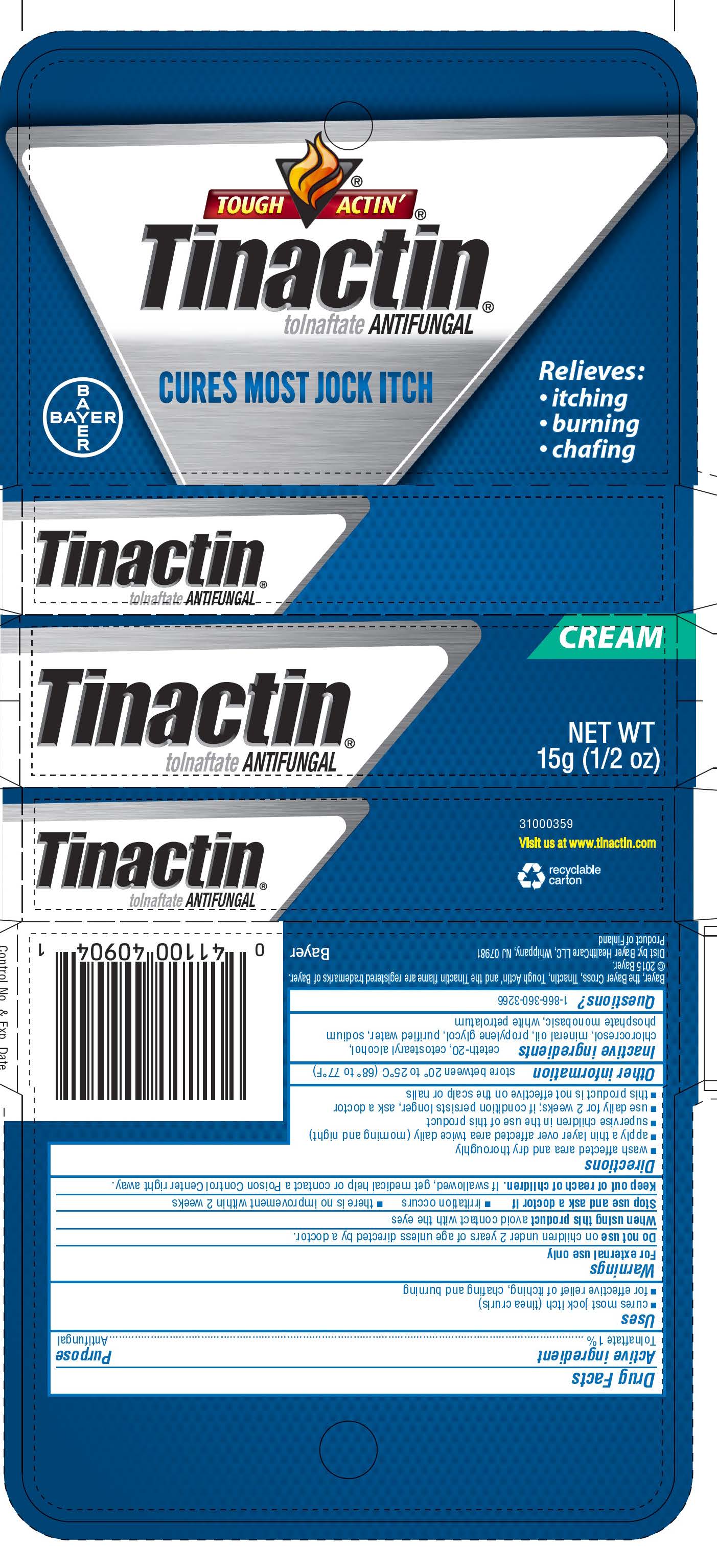 DRUG LABEL: Tinactin
NDC: 11523-0934 | Form: CREAM
Manufacturer: Bayer HealthCare LLC.
Category: otc | Type: HUMAN OTC DRUG LABEL
Date: 20251204

ACTIVE INGREDIENTS: TOLNAFTATE 10 mg/1 g
INACTIVE INGREDIENTS: CETETH-20; CETOSTEARYL ALCOHOL; CHLOROCRESOL; MINERAL OIL; PROPYLENE GLYCOL; WATER; SODIUM PHOSPHATE, MONOBASIC; PETROLATUM

Tinactin® Jock Itch

Drug Facts

Active ingredient

Tolnaftate 1%

Purpose

Antifungal

Uses

- cures most jock itch (tinea cruris)
- for effective relief of itching, chafing and burning

Warnings

For external use only

Do not use on children under 2 years of age except under the advice and supervision of a doctor.

When using this product avoid contact with the eyes

Stop use and ask a doctor if

- irritation occurs
- there is no improvement within 2 weeks

Keep out of reach of children. If swallowed, get medical help or contact a Poison Control Center right away.

Directions

- wash affected area and dry thoroughly
- apply a thin layer over affected area twice daily (morning and night)
- supervise children in the use of this product
- use daily for 2 weeks; if condition persists longer, ask a doctor
- this product is not effective on the scalp or nails

Other information

store between 20° to 25°C (68° to 77°F)

Inactive ingredients

ceteth-20, cetostearyl alcohol, chlorocresol, mineral oil, propylene glycol, purified water, sodium phosphate monobasic, white petrolatum

Questions?

1-866-360-3266

Distributed by Bayer Healthcare LLC, Whippany, NJ, USA, 07981.

PRINCIPAL DISPLAY PANEL - 15g Tube Carton

TOUCH ACTIN'

Tinactin®
tolnaftate ANTIFUNGAL
CURES MOST JOCK ITCH
ANTIFUNGAL

CREAM

Relieves:

- itching
- burning
- chafing

NET WT
15g (1/2 oz)